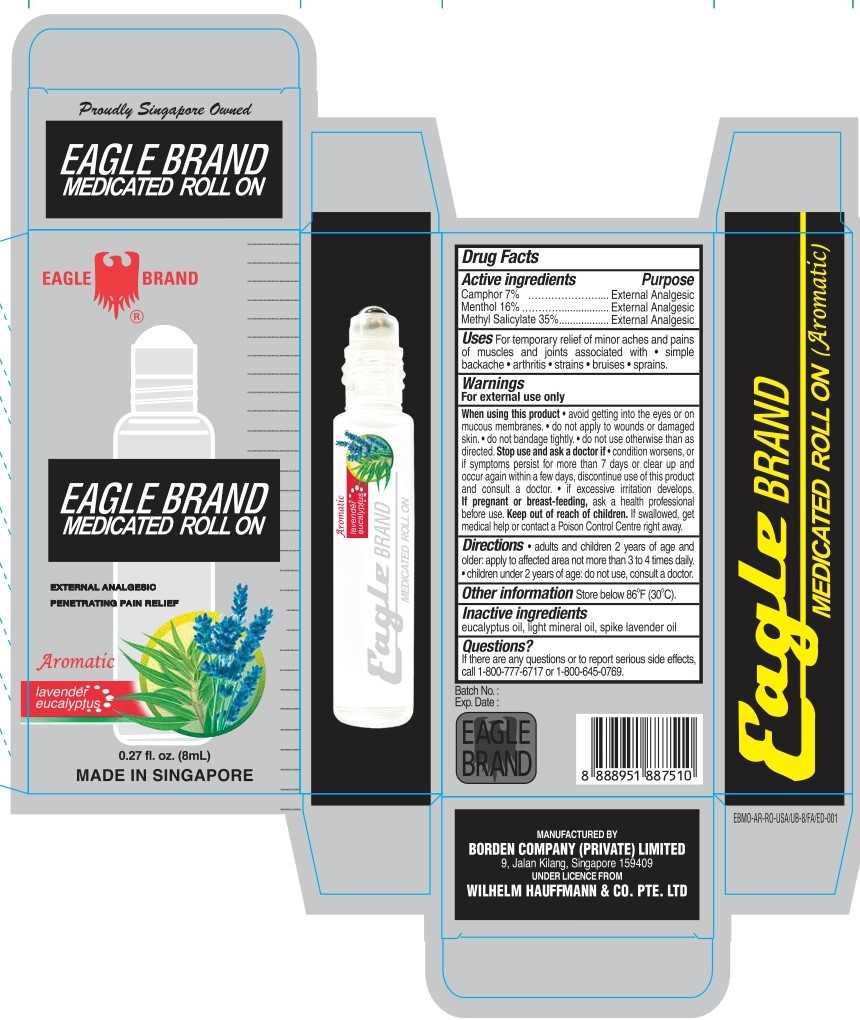 DRUG LABEL: Eagle Brand
NDC: 43405-017 | Form: OIL
Manufacturer: Borden Company (Private) Limited
Category: otc | Type: HUMAN OTC DRUG LABEL
Date: 20250120

ACTIVE INGREDIENTS: METHYL SALICYLATE 35 g/100 mL; CAMPHOR (SYNTHETIC) 7 g/100 mL; MENTHOL 16 g/100 mL
INACTIVE INGREDIENTS: LIGHT MINERAL OIL; SPIKE LAVENDER OIL; EUCALYPTUS OIL

Eagle Brand Medicated Roll On Aromatic

Active ingredients

- Camphor 7%
- Menthol 16%
- Methyl Salicylate 35%

Purpose

External Analgesic

Uses

For temporary relief of minor aches and pains of muscles and joints associated with • simple backache • arthritis • strains • bruises • sprains.

Warnings

For external use only

When using this product

- Avoid getting into the eyes or on mucous membranes.
- Do not apply to wounds or damaged skin.
- Do not bandage tightly.
- Do not use otherwise than as directed.

Stop use and ask doctor if

- Condition worsens, or if symptoms persist for more than 7 days or clear up and occur again within a few days, discontinue use of this product and consult a doctor.
- Excessive skin irritation develops.

If pregnant or breast-feeding

Ask a health professional before use.

Keep out of reach of children

If swallowed, get medical help or contact a Poison Control Centre right away.

Directions

- Adults and children 2 years of age and older:apply to affected area not more than 3 to 4 times daily.
- Children under 2 years of age: do not use, consult a doctor.

Other information

Store below 86oF (30oC).

Inactive ingredients

Eucalyptus oil, light mineral oil, spike lavender oil

Questions?

If there are any questions or to report serious side effects, call 1-800-777-6717 or 1-800-645-0769.

Package Label

8ml NDC: 43405-017-08